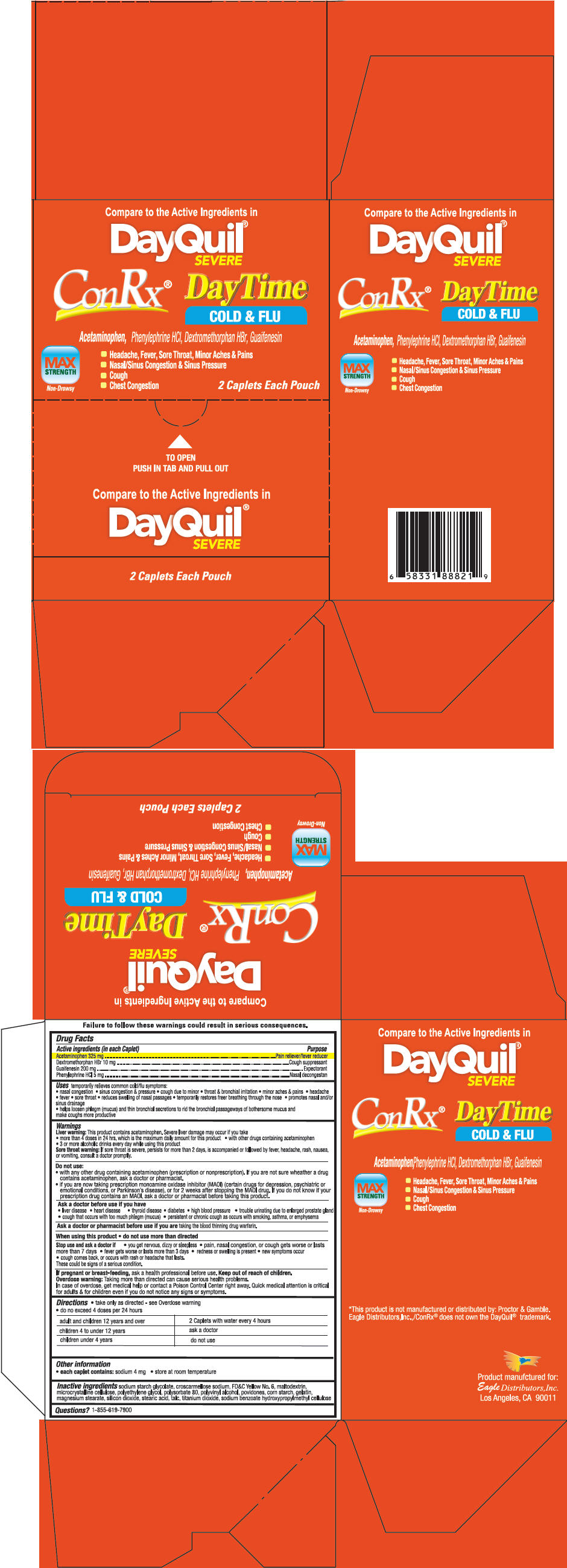 DRUG LABEL: ConRX DayTime
NDC: 68737-238 | Form: TABLET
Manufacturer: Eagle Distributors,Inc
Category: otc | Type: HUMAN OTC DRUG LABEL
Date: 20140121

ACTIVE INGREDIENTS: Phenylephrine Hydrochloride 5 mg/1 1; Acetaminophen 325 mg/1 1; DEXTROMETHORPHAN HYDROBROMIDE 10 mg/1 1; Guaifenesin 200 mg/1 1
INACTIVE INGREDIENTS: CROSCARMELLOSE SODIUM; FD&C YELLOW NO. 6; Maltodextrin; Cellulose, Microcrystalline; Polysorbate 80; Povidones; Polyethylene Glycols; Silicon dioxide; Talc; Titanium dioxide; Stearic Acid; Polyvinyl Alcohol; Starch, Corn; Gelatin; Magnesium Stearate; SODIUM STARCH GLYCOLATE TYPE A CORN; Sodium Benzoate; HYPROMELLOSES

ConRX® DayTime

Drug Facts

ACTIVE INGREDIENT

Active ingredients (in each Caple | Purpose
Acetaminophen 325 mg | Pain reliever/fever reducer
Dextromethorphan HBr 10 mg | Cough suppressant
Guaifenesin 200 mg | Expectorant
Phenylephrine HCl 5 mg | Nasal decongestan

Uses

temporarily relieves common cold/flu symptoms:

- nasal congestion
- sinus congestion & pressure
- cough due to minor
- throat & bronchial irritation
- minor aches & pains
- headache
- fever
- sore throat
- reduces swelling of nasal passages
- temporarily restores freer breathing through the nose
- promotes nasal and/or sinus drainage
- helps loosen phlegm (mucus) and thin bronchial secretions to rid the bronchial passageways of bothersome mucus and make coughs more productive

Warnings

Liver warning

This product contains acetaminophen. Severe liver damage may occur if you take

- more than 4 doses in 24 hrs, which is the maximum daily amount for this product
- with other drugs containing acetaminophen
- 3 or more alcoholic drinks every day while using this product

Sore throat warning

If sore throat is severe, persists for more than 2 days, is accompanied or followed by fever, headache, rash, nausea, or vomiting, consult a doctor promptly.

Do not use

- with any other drug containing acetaminophen (prescription or nonprescription). If you are not sure wheather a drug contains acetaminophen, ask a doctor or pharmacist.
- if you are now taking prescription monoamine oxidase inhibitor (MAOI) (certain drugs for depression, psychiatric or emotional conditions, or Parkinson's disease), or for 2 weeks after stopping the MAOI drug. If you do not know if your prescription drug contains an MAOI, ask a doctor or pharmacist before taking this product.

Ask a doctor before use if you have

- liver disease
- heart disease
- thyroid disease
- diabetes
- high blood pressure
- trouble urinating due to enlarged prostate gland
- cough that occurs with too much phlegm (mucus)
- persistent or chronic cough as occurs with smoking, asthma, or emphysema

Ask a doctor or pharmacist before use if you are taking the blood thinning drug warfarin.

When using this product

- do not use more than directed

Stop use and ask a doctor if

- you get nervous, dizzy or sleepless
- pain, nasal congestion, or cough gets worse or lasts more than 7 days
- fever gets worse or lasts more than 3 days
- redness or swelling is present
- new symptoms occur
- cough comes back, or occurs with rash or headache that lasts. These could be signs of a serious condition.

PREGNANCY OR BREAST FEEDING

If pregnant or breast-feeding, ask a health professional before use.

Keep out of reach of children.

Overdose warning

Taking more than directed can cause serious health problems. In case of overdose, get medical help or contact a Poison Control Center right away. Quick medical attention is critical for adults & for children even if you do not notice any signs or symptoms.

Directions

- take only as directed - see Overdose warning
- do no exceed 4 doses per 24 hours
  adult and children 12 years and over, 2 Caplets with water every 4 hours
  children 4 to under 12 years, ask a doctor
  children under 4 years, do not use

Other information

- each caplet contains: sodium 4 mg
- store at room temperature

Inactive ingredients

sodium starch glycolate, croscarmellose sodium, FD&C Yellow No. 6, maltodextrin, microcrystalline cellulose, polyethylene glycol, polysorbate 80, polyvinyl alcohol, povidones, corn starch, gelatin, magnesium stearate, silicon dioxide, stearic acid, talc, titanium dioxide, sodium benzoate hydroxypropylmethyl cellulose

Questions?

1-855-619-7900

PRINCIPAL DISPLAY PANEL - 50 x 2 Caplet Pouch Box

Compare to the Active Ingredients in
DayQuil®
SEVERE

ConRx®

DayTime
COLD & FLU

Acetaminophen, Phenylephrine HCl, Dextromethorphan HBr, Guaifenesin

MAX
STRENGTH

Non-Drowsy

- Headache, Fever, Sore Throat, Minor Aches & Pains
- Nasal/Sinus Congestion & Sinus Pressure
- Cough
- Chest Congestion

2 Caplets Each Pouch

TO OPEN
PUSH IN TAB AND PULL OUT

Compare to the Active Ingredients in
DayQuil®
SEVERE

2 Caplets Each Pouch